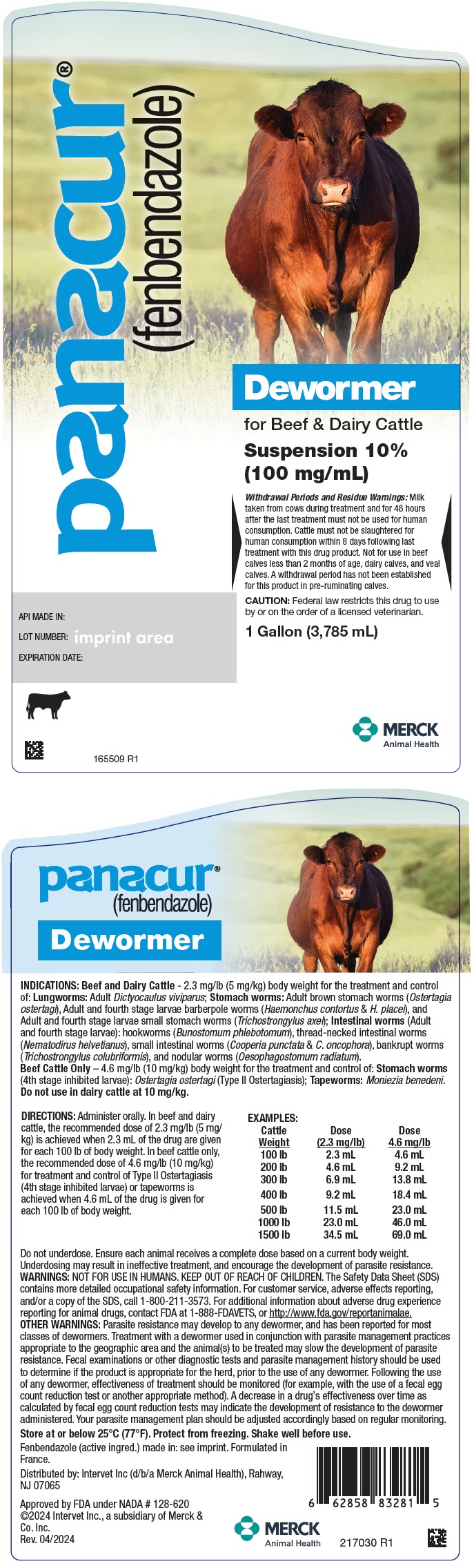 DRUG LABEL: Panacur
NDC: 57926-086 | Form: SUSPENSION
Manufacturer: Merck Sharp & Dohme Corp.
Category: animal | Type: PRESCRIPTION ANIMAL DRUG LABEL
Date: 20241115

ACTIVE INGREDIENTS: FENBENDAZOLE 100 mg/1 mL

panacur®
(fenbendazole)
Dewormer

VETERINARY INDICATIONS

INDICATIONS: Beef and Dairy Cattle - 2.3 mg/lb (5 mg/kg) body weight for the treatment and control of: Lungworms: Adult Dictyocaulus viviparus; Stomach worms: Adult brown stomach worms (Ostertagia ostertagi), Adult and fourth stage larvae barberpole worms (Haemonchus contortus & H. placei), and Adult and fourth stage larvae small stomach worms (Trichostrongylus axei); Intestinal worms (Adult and fourth stage larvae): hookworms (Bunostomum phlebotomum), thread-necked intestinal worms (Nematodirus helvetianus), small intestinal worms (Cooperia punctata & C. oncophora), bankrupt worms (Trichostrongylus colubriformis), and nodular worms (Oesophagostomum radiatum).

Beef Cattle Only – 4.6 mg/lb (10 mg/kg) body weight for the treatment and control of: Stomach worms (4th stage inhibited larvae): Ostertagia ostertagi (Type II Ostertagiasis); Tapeworms: Moniezia benedeni.

Do not use in dairy cattle at 10 mg/kg.

DOSAGE AND ADMINISTRATION

DIRECTIONS: Administer orally. In beef and dairy cattle, the recommended dose of 2.3 mg/lb (5 mg/ kg) is achieved when 2.3 mL of the drug are given for each 100 lb of body weight. In beef cattle only, the recommended dose of 4.6 mg/lb (10 mg/kg) for treatment and control of Type II Ostertagiasis (4th stage inhibited larvae) or tapeworms is achieved when 4.6 mL of the drug is given for each 100 lb of body weight.

EXAMPLES:

Cattle Weight | Dose (2.3 mg/lb) | Dose 4.6 mg/lb
100 lb | 2.3 mL | 4.6 mL
200 lb | 4.6 mL | 9.2 mL
300 lb | 6.9 mL | 13.8 mL
400 lb | 9.2 mL | 18.4 mL
500 lb | 11.5 mL | 23.0 mL
1000 lb | 23.0 mL | 46.0 mL
1500 lb | 34.5 mL | 69.0 mL

Do not underdose. Ensure each animal receives a complete dose based on a current body weight. Underdosing may result in ineffective treatment, and encourage the development of parasite resistance.

WARNINGS

WARNINGS: NOT FOR USE IN HUMANS. KEEP OUT OF REACH OF CHILDREN. The Safety Data Sheet (SDS) contains more detailed occupational safety information. For customer service, adverse effects reporting, and/or a copy of the SDS, call 1-800-211-3573. For additional information about adverse drug experience reporting for animal drugs, contact FDA at 1-888-FDAVETS, or http://www.fda.gov/reportanimalae.

WARNINGS

OTHER WARNINGS: Parasite resistance may develop to any dewormer, and has been reported for most classes of dewormers. Treatment with a dewormer used in conjunction with parasite management practices appropriate to the geographic area and the animal(s) to be treated may slow the development of parasite resistance. Fecal examinations or other diagnostic tests and parasite management history should be used to determine if the product is appropriate for the herd, prior to the use of any dewormer. Following the use of any dewormer, effectiveness of treatment should be monitored (for example, with the use of a fecal egg count reduction test or another appropriate method). A decrease in a drug's effectiveness over time as calculated by fecal egg count reduction tests may indicate the development of resistance to the dewormer administered. Your parasite management plan should be adjusted accordingly based on regular monitoring.

STORAGE AND HANDLING

Store at or below 25°C (77°F). Protect from freezing. Shake well before use.

Fenbendazole (active ingred.) made in: see imprint. Formulated in France.

Distributed by: Intervet Inc (d/b/a Merck Animal Health), Rahway, NJ 07065

Approved by FDA under NADA # 128-620
©2024 Intervet Inc., a subsidiary of Merck & Co. Inc.
Rev. 04/2024

217030 R1

PRINCIPAL DISPLAY PANEL - 1 Gallon (3785 mL) Bottle Label

panacur®
(fenbendazole)

Dewormer
for Beef & Dairy Cattle

Suspension 10%
(100 mg/mL)

Withdrawal Periods and Residue Warnings: Milk
taken from cows during treatment and for 48 hours
after the last treatment must not be used for human
consumption. Cattle must not be slaughtered for
human consumption within 8 days following last
treatment with this drug product. Not for use in beef
calves less than 2 months of age, dairy calves, and veal
calves. A withdrawal period has not been established
for this product in pre-ruminating calves.

CAUTION: Federal law restricts this drug to use
by or on the order of a licensed veterinarian.

1 Gallon (3,785 mL)

API MADE IN:

LOT NUMBER:

EXPIRATION DATE:

MERCK
Animal Health

165509 R1